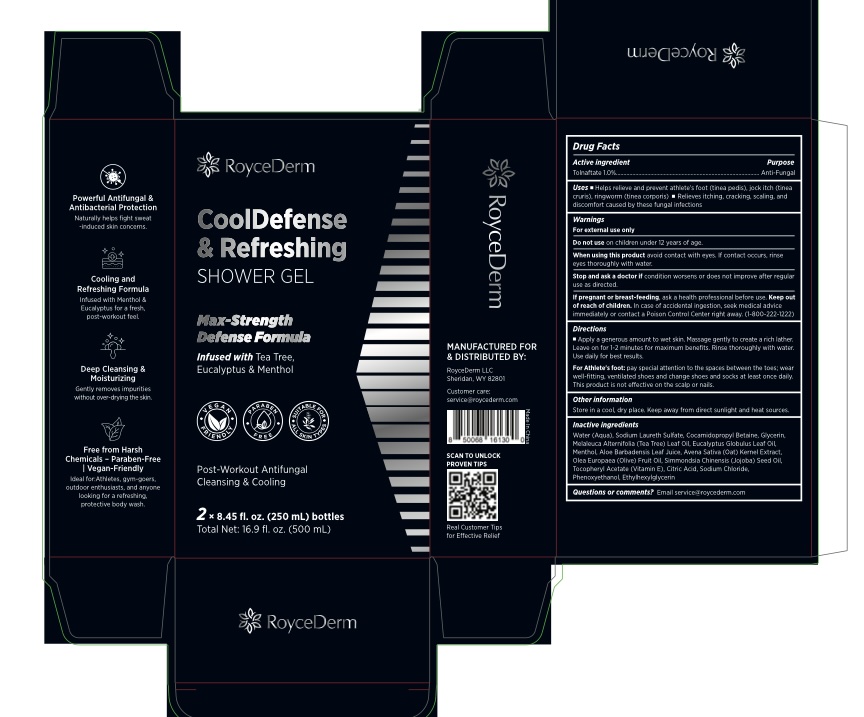 DRUG LABEL: RoyceDerm CoolDefense Refreshing Shower Gel
NDC: 85424-007 | Form: LIQUID
Manufacturer: RoyceDerm LLC
Category: otc | Type: HUMAN OTC DRUG LABEL
Date: 20250731

ACTIVE INGREDIENTS: TOLNAFTATE 1 g/100 mL
INACTIVE INGREDIENTS: ALOE BARBADENSIS LEAF JUICE; AQUA; EUCALYPTUS GLOBULUS LEAF OIL; AVENA SATIVA (OAT) KERNEL OIL; COCAMIDOPROPYL BETAINE; SODIUM LAURETH SULFATE; PHENOXYETHANOL; CITRIC ACID; GLYCERIN; OLEA EUROPAEA (OLIVE) FRUIT OIL; SODIUM CHLORIDE; MENTHOL; ETHYLHEXYLGLYCERIN; .ALPHA.-TOCOPHEROL ACETATE; MELALEUCA ALTERNIFOLIA (TEA TREE) LEAF OIL; SIMMONDSIA CHINENSIS (JOJOBA) SEED OIL

Initial Drug Listing - RoyceDerm CoolDefense & Refreshing SHOWER GEL

ACTIVE INGREDIENT

Tolnaftate 1.0%

PURPOSE

anti-fungal

INDICATIONS AND USAGE

- Helps relieve and prevent athlete's foot (tinea pedis), jock itch (tinea cruris), ringworm (tinea corporis)
- Relieves itching, cracking, scaling, and discomfort caused by these fungal infections.

WARNINGS

For external use only

DO NOT USE

on children under 12 years of age.

When using this product avoid contact with eyes. If contact occurs, rinse eyes thoroughly with water.

Stop use and ask a doctor if condition worsens or does not improve after regular use as directed.

PREGNANCY OR BREAST FEEDING

If pregnancy or breast feeding, ask a health professional before use.

Keep out of reach of Children. In case of accidental ingestion, seek medical advice immediately or contact a poison control center right away.

DOSAGE AND ADMINISTRATION

- Apply a generous amount to wet skin.
- Massage gently to create a rich lather.
- Leave on for 1-2 minutes for maximum benefits.
- Rinse thoroughly with water.
- Use daily for best results.
- For Athlete's foot: pay special attention to the spaces between the toes; wear well-fitting, ventilated shoes and change shoes and socks at least once daily.
- This product is not effective on the scalp or nails.

OTHER SAFETY INFORMATION

Store in a cool, dry place. Keep away from direct sunlight and heat sources.

INACTIVE INGREDIENT

Water (Aqua), Sodium Laureth Sulfate, Cocamidopropyl Betaine, Glycerin, Melaleuca Alternifolia (Tea Tree) Leaf Oil, Eucalyptus Globulus Leaf Oil, Menthol, Aloe Barbadensis Leaf Juice, Avena Sativa (Oat) Kernel Extract, Olea Europaea (Olive) Fruit Oil, Simmondsia Chinensis (Jojoba) Seed Oil, Tocopheryl Acetate (Vitamin E), Citric Acid, Sodium Chloride, Phenoxyethanol, Ethylhexylglycerin

QUESTIONS

Email service@roycederm.com